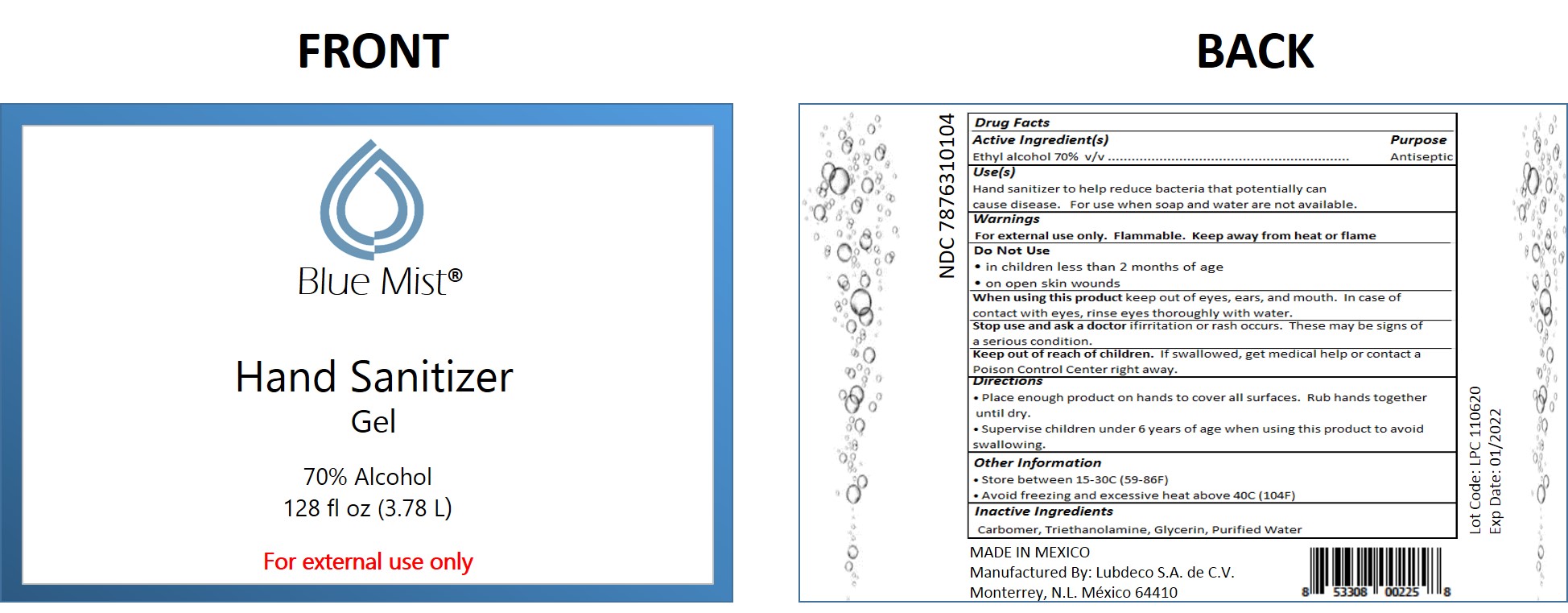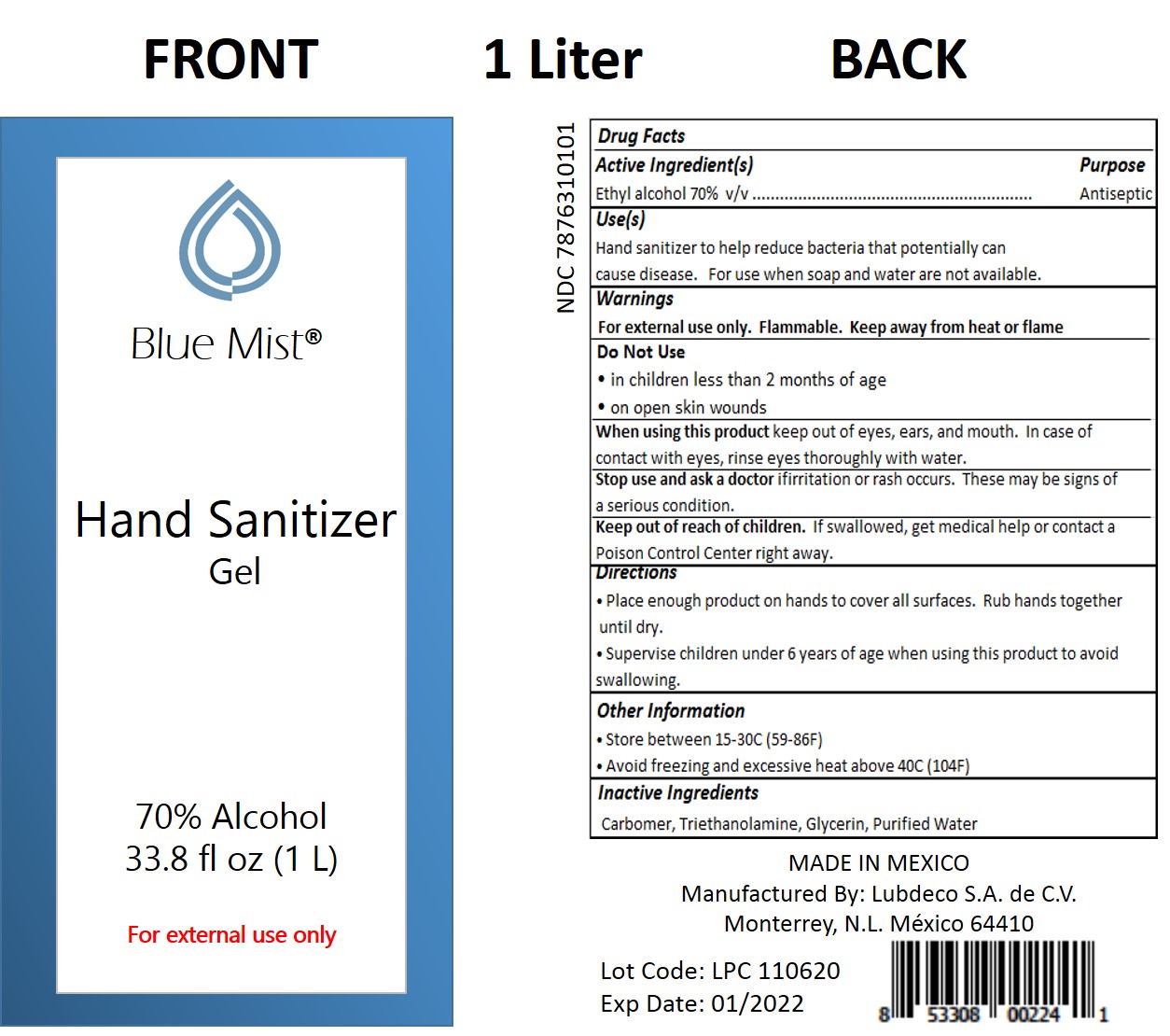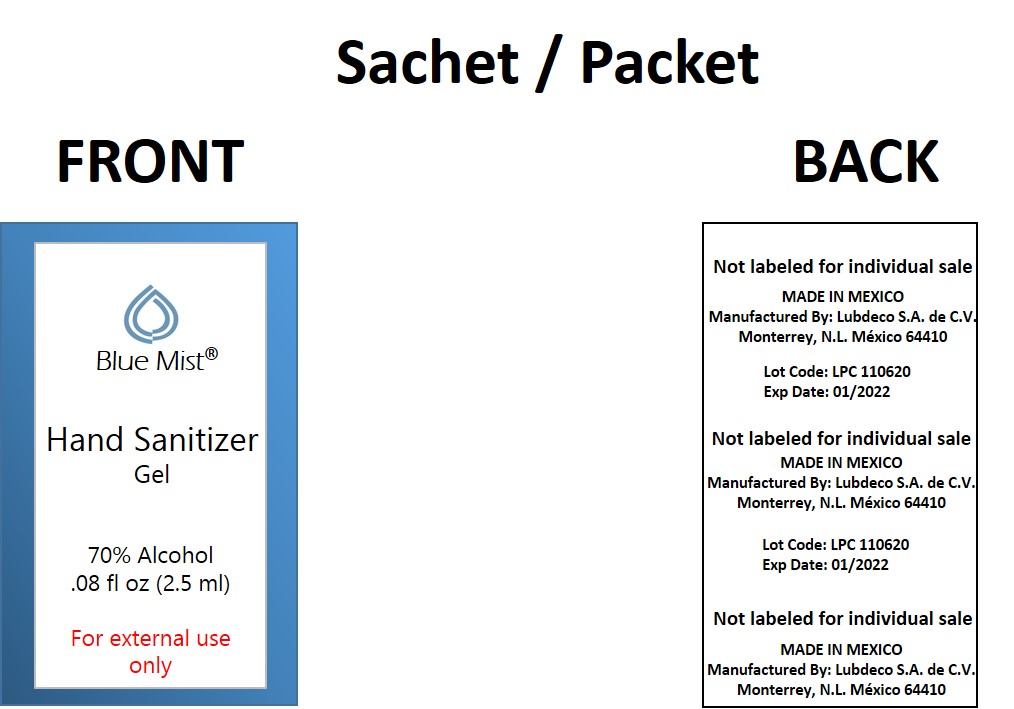 DRUG LABEL: Hand Sanitizer
NDC: 78763-101 | Form: LIQUID
Manufacturer: Lubdeco S.A. de C.V.
Category: otc | Type: HUMAN OTC DRUG LABEL
Date: 20200903

ACTIVE INGREDIENTS: ALCOHOL 700 mL/1000 mL
INACTIVE INGREDIENTS: TRIETHANOLAMINE LAURYL SULFATE; GLYCERIN; CARBOMER HOMOPOLYMER TYPE B (ALLYL PENTAERYTHRITOL CROSSLINKED); WATER

Hand Sanitizer

DOSAGE AND ADMINISTRATION

Hand Sanitizer to help reduce bacteria that potentially can cause disease. For use when soap and water are not available.

ACTIVE INGREDIENT

Alcohol 70% v/v. Purpose: Antiseptic

INACTIVE INGREDIENT

Carbomer

Triethanolamine

Glycerin

Purified Water

INDICATIONS AND USAGE

Place enough product on hands to cover all surfaces. Rub hands together until dry.

Supervise children under 6 years of age using this product to avoid swallowing.

Keep out of reach of children. If swallowed, get medical help or contact a Poison Control Center right away.

PURPOSE

Antiseptic

WARNINGS

For external use only. Flammable. Keep away from fire or flame

PACKAGE LABEL

1L NDC: 78763-101-01

3.78L NDC: 78763-101-04

2.5ml NDC: 78763-101-99